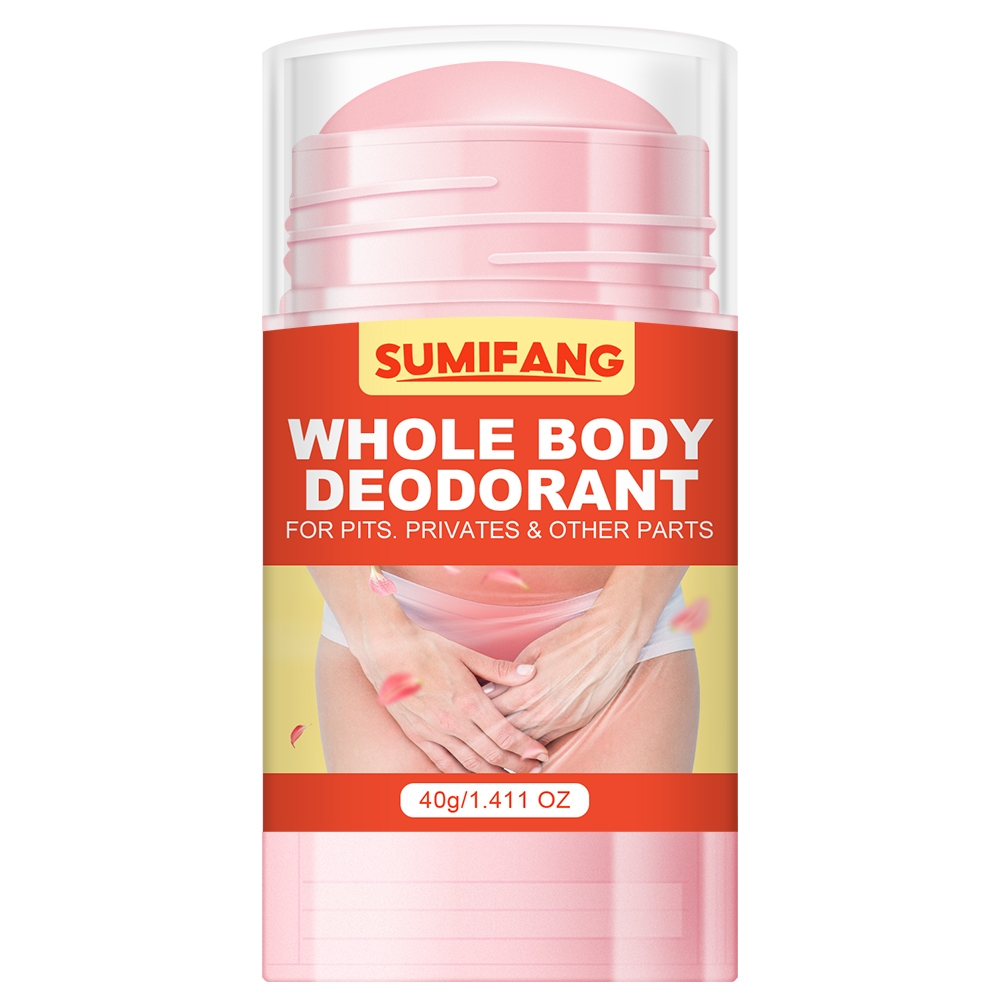 DRUG LABEL: WHOLE BODY DEODORANT
NDC: 84025-234 | Form: CREAM
Manufacturer: Guangzhou Yanxi Biotechnology Co., Ltd
Category: otc | Type: HUMAN OTC DRUG LABEL
Date: 20241025

ACTIVE INGREDIENTS: HYDROGENATED AVOCADO OIL 3 mg/100 mL; MINERAL OIL 5 mg/100 mL
INACTIVE INGREDIENTS: WATER

DOSAGE AND ADMINISTRATION

1.Wipe clean the body afterbathing. 2.Apply it to the place
wherebrighten is needed, it can be used all overthe body. 3.Gently massage into
skin untilfully absorbed.Warning: 1. For external use only.

WARNINGS

Keep out of children

INACTIVE INGREDIENT

Aqua

INDICATIONS AND USAGE

for daily body care

keep out of children

PURPOSE

Eliminate body odor